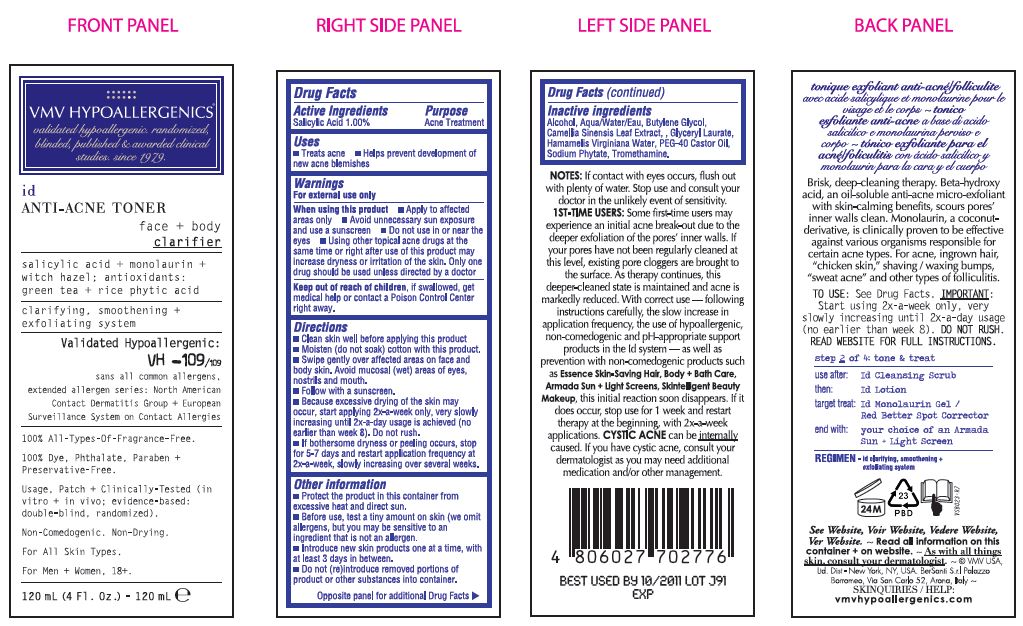 DRUG LABEL: ID Anti-Acne Toner Clarifying Face Plus Body Treatment
NDC: 69774-552 | Form: LIQUID
Manufacturer: SKIN SCIENCES LABORATORY INC.
Category: otc | Type: HUMAN OTC DRUG LABEL
Date: 20170515

ACTIVE INGREDIENTS: SALICYLIC ACID 1.2 g/120 mL
INACTIVE INGREDIENTS: TROMETHAMINE; GLYCERYL LAURATE; WATER; BUTYLENE GLYCOL; CASTOR OIL; ALCOHOL; HAMAMELIS VIRGINIANA TOP WATER; PHYTATE SODIUM

ID Anti-Acne Toner Clarifying Face + Body Treatment

Active Ingredients
Salicylic Acid 1.00%

Purpose
Acne Treatment

Purpose
Acne Treatment

Uses
- Treats acne
- Hepls prevent development of new acne blemishes

Warnings

For external use only

When using this product
- Apply to affected areas only
- Avoid unnecessary sun exposure and use a sunscreen
- Do not use in or near the eyes
- Using other topical acne drugs at the same time
or right after use of this product
may increase dryness or irritation of the skin.
Only one drug should be used unless directed by a doctor

Keep out of reach of children, if
swallowed, get medical help or contact a Poison Control Center
right away.

Keep out of reach of children, if
swallowed, get medical help or contact a Poison Control Center
right away.

Directions
- Clean skin well before applying this product
- Moisten (do not soak) cotton with this product.
- Swipe gently over affected areas on face and
body skin. Avoid mucosal (wet) areas of eyes,
nostrils and mouth
- Follow with a sunscreen
- Because excessive drying of the skin may
occur, start applying 2x-a-week only, very slowly
increasing until 2x-a-day usage is achieved (no
earlier than week 8). Do not rush.
- If bothersome dryness or peeling occurs, stop
for 5-7 days and restart application frequency at
2x-a-week, slowly increasing over several weeks.

STORAGE AND HANDLING

- Protect the product in this container from excessive heat and direct sun.
- Before use, test a tiny amount on skin (we omit allergens, but you may be sensitive
to an ingredient that is not an allergen.
- Introduce new skin products one at a time, with at least 3 days in between.
- Do not (re)introduce removed portions of product or other substances into container.

Inactive ingredients
Alcohol, Aqua/Water/Eau, Butylene Glycol,
Camellia Sinensis Leaf Extract, Gyceryl Laurate,
Hamamelis Virginiana Water, PEG-40 Castor Oil,
Sodium Phytate, Tromethamine

OTHER SAFETY INFORMATION

Notes: If contact with eyes
occurs, flush out with plenty of
water. This product is meant to be washed off quickly, not left on the
skin for longer than a few seconds
while cleansing. Prolonged
exposure without rinsing
immediately may cause irritation to
skin. Stop use and consult your
doctor in the unlikely event of
discomfort or sensitivity. 1ST-TIME
USERS: Some first-time users may
experience an initial acne
break-out due to the deeper
exfoliation of the pores' inner
walls. If your pores have not been
regularly cleaned at this level,
existing pore cloggers are brought
to the surface. As therapy
continues, this deeper-cleaned
state is maintained and acne is
markedly reduced. With correct
use - following instructions
carefully, the slow increase in
application frequency, the use of
hypoallergenic, non-comedogenic
and pH-appropriate support
products in the Id system - as well
as prevention with non-comedo-
genic products such as Essence
Skin-Saving Hair, Body + Bath Care,
Armada Sun + Light Screens,
Skintelligent Beauty Makeup, this
initial reaction soon disappears. If it
does occur, stop use for 1 week
and restart therapy at the
beginning, with 2x-a-week
applications. CYSTIC ACNE can
be internally caused. If you have
cystic acne, consult your
dermatologist as you may need
additional medication and/or other
management.

PACKAGE LABEL

ID TONER

VMV HYPOALLERGENICS
validated hypoallergenic.
randomized, blinded, published &
awarded clinical studies. since 1979

Id
ANTI-ACNE TONER
Face + body
Clarifier

Salicylic acid + monolaurin + witch hazel;
antioxidants : green tea + rice phytic acid
clarifying , smoothening + exfoliating system

Validated
Hypoallergenic:
VH -109/109
sans all common allergens,
extended allergen series:
North American Contact Dermatitis
Group + European Surveillance
System on Contact Allergies

100% All-Types-Of-Fragrance-Free.

100% Dye, Phthalate, Paraben + Preservative-Free.

Usage, Patch + Clinically-Tested (in vitro + in vivo; evidence-based:
double-blind, randomized).

Non-Comedogenic. Non-Drying.

For All Skin Types.

For Men + Women, 18+.

120 mL (4 Fl. Oz.) - 120 mL